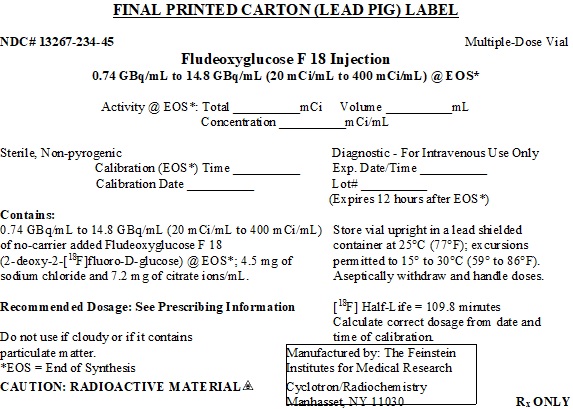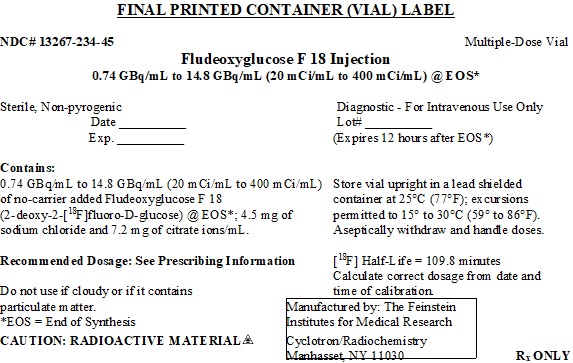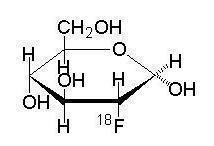 DRUG LABEL: Fludeoxyglucose
NDC: 13267-234 | Form: INJECTION
Manufacturer: THE FEINSTEIN INSTITUTE FOR MEDICAL RESEARCH
Category: prescription | Type: HUMAN PRESCRIPTION DRUG LABEL
Date: 20190711

ACTIVE INGREDIENTS: FLUDEOXYGLUCOSE F-18 400 mCi/1 mL

HIGHLIGHTS OF PRESCRIBING INFORMATION

These highlights do not include all the information needed to use Fludeoxyglucose F 18 Injection safely and effectively. See full prescribing information for Fludeoxyglucose F 18 Injection.
Fludeoxyglucose F 18 Injection, for intravenous use
Initial U.S. Approval: 2005

1 INDICATIONS AND USAGE

Fludeoxyglucose F 18 Injection is indicated for positron emission tomography (PET) imaging in the following settings:

- Oncology: For assessment of abnormal glucose metabolism to assist in the evaluation of malignancy in patients with known or suspected abnormalities found by other testing modalities, or in patients with an existing diagnosis of cancer.
- Cardiology: For the identification of left ventricular myocardium with residual glucose metabolism and reversible loss of systolic function in patients with coronary artery disease and left ventricular dysfunction, when used together with myocardial perfusion imaging.
- Neurology: For the identification of regions of abnormal glucose metabolism associated with foci of epileptic seizures (1).

2 DOSAGE AND ADMINISTRATION

Fludeoxyglucose F 18 Injection emits radiation. Use procedures to minimize radiation exposure. Screen for blood glucose abnormalities.

- In the oncology and neurology settings, instruct patients to fast for 4 – 6 hours prior to the drug’s injection. Consider medical therapy and laboratory testing to assure at least two days of normoglycemia prior to the drug’s administration (5.2).
- In the cardiology setting, administration of glucose-containing food or liquids (e.g., 50 – 75 grams) prior to the drug’s injection facilitates localization of cardiac ischemia (2.3).

Aseptically withdraw Fludeoxyglucose F 18 Injection from its container and administer by intravenous injection (2). The recommended dose:

- for adults is 5 – 10 mCi (185 – 370 MBq), in all indicated clinical settings (2.1).
- for pediatric patients is 2.6 mCi (96.2 MBq) in the neurology setting (2.2).

Initiate imaging within 40 minutes following drug injection; acquire static emission images 30 – 100 minutes from time of injection (2).

3 DOSAGE FORMS AND STRENGTHS

Multiple-dose glass vial containing 0.74 – 14.8 GBq/mL (20 – 400 mCi/mL) of Fludeoxyglucose F 18 Injection, 4.5 mg of sodium chloride, and 7.2 mg of citrate ions/mL (approximately 20 – 22 mL volume) for intravenous administration (3).

4 CONTRAINDICATIONS

None

5 WARNINGS AND PRECAUTIONS

- Radiation risks: use smallest dose necessary for imaging (5.1).
- Blood glucose abnormalities: may cause suboptimal imaging (5.2).

6 ADVERSE REACTIONS

Hypersensitivity reactions have occurred; have emergency resuscitation equipment and personnel immediately available (6).

To report SUSPECTED ADVERSE REACTIONS, contact The Feinstein Institute for Medical Research at 516-562-1042 or FDA at 1-800-FDA-1088 or www.fda.gov/medwatch.

8 USE IN SPECIAL POPULATIONS

- Lactation: Temporarily discontinue breastfeeding. A lactating woman should pump and discard breastmilk for 9 hours after Fludeoxyglucose F 18 Injection (8.2).
- Pediatric Use: Safety and effectiveness in pediatric patients have not been established in the oncology and cardiology settings (8.4).

FULL PRESCRIBING INFORMATION

1 INDICATIONS AND USAGE

Fludeoxyglucose F 18 Injection is indicated for positron emission tomography (PET) imaging in the following settings:

1.1 Oncology

For assessment of abnormal glucose metabolism to assist in the evaluation of malignancy in patients with known or suspected abnormalities found by other testing modalities, or in patients with an existing diagnosis of cancer.

1.2 Cardiology

For the identification of left ventricular myocardium with residual glucose metabolism and reversible loss of systolic function in patients with coronary artery disease and left ventricular dysfunction, when used together with myocardial perfusion imaging.

1.3 Neurology

For the identification of regions of abnormal glucose metabolism associated with foci of epileptic seizures.

2 DOSAGE AND ADMINISTRATION

Fludeoxyglucose F 18 Injection emits radiation. Use procedures to minimize radiation exposure. Calculate the final dose from the end of synthesis (EOS) time using proper radioactive decay factors. Assay the final dose in a properly calibrated dose calibrator before administration to the patient [see Description (11.2)].

2.1 Recommended Dose for Adults

Within the oncology, cardiology and neurology settings, the recommended dose for adults is 5 – 10 mCi (185 – 370 MBq) as an intravenous injection.

2.2 Recommended Dose for Pediatric Patients

Within the neurology setting, the recommended dose for pediatric patients is 2.6 mCi, as an intravenous injection. The optimal dose adjustment on the basis of body size or weight has not been determined [see Use in Special Populations (8.4)].

2.3 Patient Preparation

- To minimize the radiation absorbed dose to the bladder, encourage adequate hydration. Encourage the patient to drink water or other fluids (as tolerated) in the 4 hours before their PET study.
- Encourage the patient to void as soon as the imaging study is completed and as often as possible thereafter for at least one hour.
- Screen patients for clinically significant blood glucose abnormalities by obtaining a history and/or laboratory tests [see Warnings and Precautions (5.2)]. Prior to Fludeoxyglucose F 18 PET imaging in the oncology and neurology settings, instruct patient to fast for 4 – 6 hours prior to the drug’s injection.
- In the cardiology setting, administration of glucose-containing food or liquids (e.g., 50 – 75 grams) prior to Fludeoxyglucose F 18 Injection facilitates localization of cardiac ischemia.

2.4 Radiation Dosimetry

The estimated human absorbed radiation doses (rem/mCi) to a newborn (3.4 kg), 1-year old (9.8 kg), 5-year old (19 kg), 10-year old (32 kg), 15-year old (57 kg), and adult (70 kg) from intravenous administration of Fludeoxyglucose F 18 Injection are shown in Table 1. These estimates were calculated based on human^1 data and using the data published by the International Commission on Radiological Protection^2 for Fludeoxyglucose F 18. The dosimetry data show that there are slight variations in absorbed radiation dose for various organs in each of the age groups. These dissimilarities in absorbed radiation dose are due to developmental age variations (e.g., organ size, location, and overall metabolic rate for each age group). The identified critical organs (in descending order) across all age groups evaluated are the urinary bladder, heart, pancreas, spleen, and lungs.

Table 1. Estimated Absorbed Radiation Doses (rem/mCi) After Intravenous Administration of Fludeoxyglucose F 18 Injectiona
Organ | Newborn (3.4kg) | 1-year old (9.8kg) | 5-year old (19kg) | 10-year old (32kg) | 15-year old (57kg) | Adult (70kg)
Bladder wallb | 4.3 | 1.7 | 0.93 | 0.60 | 0.40 | 0.32
Heart wall | 2.4 | 1.2 | 0.70 | 0.44 | 0.29 | 0.22
Pancreas | 2.2 | 0.68 | 0.33 | 0.25 | 0.13 | 0.096
Spleen | 2.2 | 0.84 | 0.46 | 0.29 | 0.19 | 0.14
Lungs | 0.96 | 0.38 | 0.20 | 0.13 | 0.092 | 0.064
Kidneys | 0.81 | 0.34 | 0.19 | 0.13 | 0.089 | 0.074
Ovaries | 0.80 | 0.8 | 0.19 | 0.11 | 0.058 | 0.053
Uterus | 0.79 | 0.35 | 0.19 | 0.12 | 0.076 | 0.062
LLI wall* | 0.69 | 0.28 | 0.15 | 0.097 | 0.060 | 0.051
Liver | 0.69 | 0.31 | 0.17 | 0.11 | 0.076 | 0.058
Gallbladder wall | 0.69 | 0.26 | 0.14 | 0.093 | 0.059 | 0.049
Small intestine | 0.68 | 0.29 | 0.15 | 0.096 | 0.060 | 0.047
ULI wall** | 0.67 | 0.27 | 0.15 | 0.090 | 0.057 | 0.046
Stomach wall | 0.65 | 0.27 | 0.14 | 0.089 | 0.057 | 0.047
Adrenals | 0.65 | 0.28 | 0.15 | 0.095 | 0.061 | 0.048
Testes | 0.64 | 0.27 | 0.14 | 0.085 | 0.052 | 0.041
Red marrow | 0.62 | 0.26 | 0.14 | 0.089 | 0.057 | 0.047
Thymus | 0.61 | 0.26 | 0.14 | 0.086 | 0.056 | 0.044
Thyroid | 0.61 | 0.26 | 0.13 | 0.080 | 0.049 | 0.039
Muscle | 0.58 | 0.25 | 0.13 | 0.078 | 0.049 | 0.039
Bone surface | 0.57 | 0.24 | 0.12 | 0.079 | 0.052 | 0.041
Breast | 0.54 | 0.22 | 0.11 | 0.068 | 0.043 | 0.034
Skin | 0.49 | 0.20 | 0.10 | 0.060 | 0.037 | 0.030
Brain | 0.29 | 0.13 | 0.09 | 0.078 | 0.072 | 0.070
Other tissues | 0.59 | 0.25 | 0.13 | 0.083 | 0.052 | 0.042

aMIRDOSE 2 software was used to calculate the radiation absorbed dose.

bThe dynamic bladder model with a uniform voiding frequency of 1.5 hours was used.
*LLI = lower large intestine; **ULI = upper large intestine

2.5 Radiation Safety – Drug Handling

- Use waterproof gloves, effective radiation shielding, and appropriate safety measures when handling Fludeoxyglucose F 18 Injection to avoid unnecessary radiation exposure to the patient, occupational workers, clinical personnel and other persons.
- Radiopharmaceuticals should be used by or under the control of physicians who are qualified by specific training and experience in the safe use and handling of radionuclides, and whose experience and training have been approved by the appropriate governmental agency authorized to license the use of radionuclides.
- Calculate the final dose from the end of synthesis (EOS) time using proper radioactive decay factors. Assay the final dose in a properly calibrated dose calibrator before administration to the patient [see Description (11.2)].
- The dose of Fludeoxyglucose F 18 used in a given patient should be minimized consistent with the objectives of the procedure, and the nature of the radiation detection devices employed.

2.6 Drug Preparation and Administration

- Calculate the necessary volume to administer based on calibration time and dose.
- Aseptically withdraw Fludeoxyglucose F 18 Injection from its container.
- Inspect Fludeoxyglucose F 18 Injection visually for particulate matter and discoloration before administration, whenever solution and container permit.
- Do not administer the drug if it contains particulate matter or discoloration; dispose of these unacceptable or unused preparations in a safe manner, in compliance with applicable regulations.
- Use Fludeoxyglucose F 18 Injection within 12 hours from the EOS.

2.7 Imaging Guidelines

- Initiate imaging within 40 minutes following Fludeoxyglucose F 18 Injection administration.
- Acquire static emission images 30 – 100 minutes from the time of injection.

3 DOSAGE FORMS AND STRENGTHS

Multiple-dose glass vial containing 0.74 - 14.8 GBq/mL (20 - 400 mCi/mL) of Fludeoxyglucose F 18 Injection, 4.5 mg of sodium chloride, and 7.2 mg of citrate ions/mL (approximately 20 - 22 mL volume) for intravenous administration.

4 CONTRAINDICATIONS

None

5 WARNINGS AND PRECAUTIONS

5.1 Radiation Risks

Radiation-emitting products, including Fludeoxyglucose F 18 Injection, may increase the risk for cancer, especially in pediatric patients. Use the smallest dose necessary for imaging and ensure safe handling to protect the patient and health care worker [see Dosage and Administration (2.5)].

5.2 Blood Glucose Abnormalities

In the oncology and neurology setting, suboptimal imaging may occur in patients with inadequately regulated blood glucose levels. In these patients, consider medical therapy and laboratory testing to assure at least two days of normoglycemia prior to Fludeoxyglucose F 18 Injection administration.

6 ADVERSE REACTIONS

Hypersensitivity reactions with pruritus, edema and rash have been reported in the post-marketing setting. Have emergency resuscitation equipment and personnel immediately available.

7 DRUG INTERACTIONS

The interaction of Fludeoxyglucose F 18 Injection with other drugs taken by patients undergoing PET imaging has not been studied.

8 USE IN SPECIAL POPULATIONS

8.1 Pregnancy

Risk Summary
Data from published case series and case reports describe Fludeoxyglucose F 18 Injection crossing the placenta with uptake by the fetus (see Data). All radiopharmaceuticals have the potential to cause fetal harm depending on the fetal stage of development and the magnitude of the radiation dose. However, published studies that describe Fludeoxyglucose F 18 Injection use in pregnant women have not identified a risk of drug-associated major birth defects, miscarriage, or adverse maternal or fetal outcomes. If considering Fludeoxyglucose F 18 Injection administration to a pregnant woman, inform the patient about the potential for adverse pregnancy outcomes based on the radiation dose from Fludeoxyglucose F 18 Injection and the gestational timing of exposure.
The estimated background risk of major birth defects and miscarriage for the indicated population is unknown. All pregnancies have a background risk of birth defect, loss, or other adverse outcomes. In the U.S. general population, the estimated background risk of major birth defects and miscarriage in clinically recognized pregnancies are 2-4% and 15-20%, respectively.
Data
Human Data
Data from published case series and case reports describe Fludeoxyglucose F 18 Injection crossing the placental barrier and visualization of radioactivity throughout the body of the fetus. The estimated fetal absorbed radiation dose from the maximum labeled dose (370 MBq) of Fludeoxyglucose F 18 was 10mGy with first trimester exposure to PET alone and 20mGy with first trimester exposure to PET/CT scan combination. Long-term adverse radiation effects to a child exposed to Fludeoxyglucose F 18 Injection in utero are unknown. No adverse fetal effects or radiation-related risks have been identified for diagnostic procedures involving less than 50mGy, which represents less than 20mGy fetal doses.

8.2 Lactation

Risk Summary
A published case report and case series show the presence of Fludeoxyglucose F 18 Injection in human milk following administration. There are no data on the effects of Fludeoxyglucose F 18 Injection on the breastfed infant or the effects on milk production. Exposure of Fludeoxyglucose F 18 Injection to a breastfed infant can be minimized by temporary discontinuation of breastfeeding (see Clinical Considerations). The developmental and health benefits of breastfeeding should be considered along with the mother’s clinical need for Fludeoxyglucose F 18 Injection, any potential adverse effects on the breastfed child from Fludeoxyglucose F 18 Injection or from the underlying maternal condition.

Clinical Considerations
To decrease radiation exposure to the breastfed infant, advise a lactating woman to pump and discard breastmilk and avoid close (breast) contact with the infant for at least 9 hours after the administration of Fludeoxyglucose F 18 Injection.

8.4 Pediatric Use

The safety and effectiveness of Fludeoxyglucose F 18 Injection in pediatric patients with epilepsy is established on the basis of studies in adult and pediatric patients. In pediatric patients with epilepsy, the recommended dose is 2.6 mCi. The optimal dose adjustment on the basis of body size or weight has not been determined.

In the oncology or cardiology settings, the safety and effectiveness of Fludeoxyglucose F 18 Injection have not been established in pediatric patients.

11 DESCRIPTION

11.1 Chemical Characteristics

Fludeoxyglucose F 18 Injection is an intravenous positron emitting radiopharmaceutical that is used for diagnostic purposes in conjunction with positron emission tomography (PET) imaging. The active ingredient 2-deoxy-2-[^18F]fluoro-D-glucose has the molecular formula of C6H11^18FO5 with a molecular weight of 181.26, and has the following chemical structure:

Fludeoxyglucose F 18 Injection is provided as a ready to use intravenous sterile, pyrogen free, clear, colorless citrate buffered solution. Each mL contains between 0.74 to 14.8 GBq (20 - 400 mCi) of 2-deoxy-2-[^18F]fluoro-D-glucose at the EOS, 4.5 mg of sodium chloride, and 7.2 mg of citrate ions/mL. The pH of the solution is between 4.5 and 7.5. The solution is packaged in a multiple-dose glass vial and does not contain any preservative.

11.2 Physical Characteristics

Fluorine F 18 has a physical half-life of 109.8 minutes and decays to Oxygen O 18 (stable) by positron decay. The principal photons useful for imaging are the dual 511 keV “annihilation” gamma photons that are produced and emitted simultaneously in opposite directions when the positron interacts with an electron (Table 2).

Table 2. Principal Radiation Emission Data for Fluorine F 18
Radiation/Emission | % Per Disintegration | Mean Energy
Positron(β+) | 96.73 | 249.8 keV
Gamma(±)* | 193.46 | 511.0 keV

*Produced by positron annihilation

From: Kocher, D.C. Radioactive Decay Tables DOE/TIC-I 1026, 89 (1981)

The specific gamma ray constant (point source air kerma coefficient) for fluorine F 18 is 5.7 R/hr/mCi (1.35 x 10^-6 Gy/hr/kBq) at 1 cm. The half-value layer (HVL) for the 511 keV photons is 4 mm lead (Pb). The range of attenuation coefficients for this radionuclide as a function of lead shield thickness is shown in Table 3. For example, the interposition of an 8 mm thickness of Pb, with a coefficient of attenuation of 0.25, will decrease the external radiation by 75%.

Table 3. Radiation Attenuation of 511 keV Photons by lead (Pb) shielding
Shield thickness (Pb) mm | Coefficient of attenuation
0 | 0.00
4 | 0.50
8 | 0.25
13 | 0.10
26 | 0.01
39 | 0.001
52 | 0.0001

For use in correcting for physical decay of this radionuclide, the fractions remaining at selected intervals after calibration are shown in Table 4.

Table 4. Physical Decay Chart for Fluorine F 18
Minutes | Fraction Remaining
0* | 1.000
15 | 0.909
30 | 0.826
60 | 0.683
110 | 0.500
220 | 0.250

*calibration time

12 CLINICAL PHARMACOLOGY

12.1 Mechanism of Action

F 18 Fludeoxyglucose is a glucose analog that concentrates in cells that rely upon glucose as an energy source, or in cells whose dependence on glucose increases under pathophysiological conditions. Fludeoxyglucose F 18 is transported through the cell membrane by facilitative glucose transporter proteins and is phosphorylated within the cell to [F 18] FDG-6-phosphate by the enzyme hexokinase. Once phosphorylated it cannot exit until it is dephosphorylated by glucose-6-phosphatase. Therefore, within a given tissue or pathophysiological process, the retention and clearance of Fludeoxyglucose F 18 reflect a balance involving glucose transporter, hexokinase and glucose-6-phosphatase activities. Fludeoxyglucose F 18 is used to assess glucose metabolism.

In comparison to background activity of the specific organ or tissue type, regions of decreased or absent uptake of Fludeoxyglucose F 18 reflect the decrease or absence of glucose metabolism. Regions of increased uptake of Fludeoxyglucose F 18 reflect greater than normal rates of glucose metabolism.

12.2 Pharmacodynamics

Fludeoxyglucose F 18 Injection is rapidly distributed to all organs of the body after intravenous administration. After background clearance of Fludeoxyglucose F 18 Injection, optimal PET imaging is generally achieved between 30 to 40 minutes after administration.

In cancer, the cells are generally characterized by enhanced glucose metabolism partially due to (1) an increase in activity of glucose transporters, (2) an increased rate of phosphorylation activity, (3) a reduction of phosphatase activity or, (4) a dynamic alteration in the balance among all these processes. However, glucose metabolism of cancer as reflected by Fludeoxyglucose F 18 accumulation shows considerable variability. Depending on tumor type, stage, and location, Fludeoxyglucose F 18 accumulation may be increased, normal, or decreased. Also, inflammatory cells can have the same variability of uptake of Fludeoxyglucose F 18.

In the heart, under normal aerobic conditions, the myocardium meets the bulk of its energy requirements by oxidizing free fatty acids. Most of the exogenous glucose taken up by the myocyte is converted into glycogen. However, under ischemic conditions, the oxidation of free fatty acids decreases, exogenous glucose becomes the preferred myocardial substrate, glycolysis is stimulated, and glucose taken up by the myocyte is metabolized immediately instead of being converted into glycogen. Under these conditions, phosphorylated Fludeoxyglucose F 18 accumulates in the myocyte and can be detected with PET imaging.

In the brain, cells normally rely on aerobic metabolism. In epilepsy, the glucose metabolism varies. Generally, during a seizure, glucose metabolism increases. Interictally, the seizure focus tends to be hypometabolic.

12.3 Pharmacokinetics

Distribution: In four healthy male volunteers, receiving an intravenous administration of 30 seconds in duration, the arterial blood level profile for Fludeoxyglucose F 18 decayed triexponentially. The effective half-life ranges of the three phases were 0.2-0.3 minutes, 10-13 minutes with a mean and standard deviation (STD) of 12 ±(1) min, and 80-95 minutes with a mean and STD of 88 ± (4) min.

Plasma protein binding of Fludeoxyglucose F 18 has not been studied.

Metabolism: Fludeoxyglucose F 18 is transported into cells and phosphorylated to [F 18]-FDG-6- phosphate at a rate proportional to the rate of glucose utilization within that tissue. [F 18]-FDG-6-phosphate presumably is metabolized to 2-deoxy-2-[F 18]fluoro-6-phospho-D-mannose([F 18]FDM-6-phosphate).

Fludeoxyglucose F 18 Injection may contain several impurities (e.g., 2-deoxy-2-chloro-D-glucose (ClDG)). Biodistribution and metabolism of ClDG are presumed to be similar to Fludeoxyglucose F 18 and would be expected to result in intracellular formation of 2-deoxy-2-chloro-6-phospho-D-glucose (ClDG-6-phosphate) and 2-deoxy-2-chloro-6-phospho-D-mannose (ClDM-6-phosphate). The phosphorylated deoxyglucose compounds are dephosphorylated and the resulting compounds (FDG, FDM, ClDG, and ClDM) presumably leave cells by passive diffusion. Fludeoxyglucose F 18 and related compounds are cleared from non-cardiac tissues within 3 to 24 hours after administration. Clearance from the cardiac tissue may require more than 96 hours. Fludeoxyglucose F 18 that is not involved in glucose metabolism in any tissue is then excreted in the urine.

Elimination: Fludeoxyglucose F 18 is cleared from most tissues within 24 hours and can be eliminated from the body unchanged in the urine. Within 33 minutes, a mean of 3.9% of the administrated radioactive dose was measured in the urine. The amount of radiation exposure of the urinary bladder at two hours post-administration suggests that 20.6% (mean) of the radioactive dose was present in the bladder.

Special Populations: The pharmacokinetics of Fludeoxyglucose F 18 Injection have not been studied in renally-impaired, hepatically impaired or pediatric patients. Fludeoxyglucose F 18 is eliminated through the renal system. Avoid excessive radiation exposure to this organ system and adjacent tissues.

The effects of fasting, varying blood sugar levels, conditions of glucose intolerance, and diabetes mellitus on Fludeoxyglucose F 18 distribution in humans have not been ascertained [see Warnings and Precautions (5.2)].

13 NONCLINICAL TOXICOLOGY

13.1 Carcinogenesis, Mutagenesis, Impairment of Fertility

Animal studies have not been performed to evaluate the Fludeoxyglucose F 18 Injection carcinogenic potential, mutagenic potential or effects on fertility.

14 CLINICAL STUDIES

14.1 Oncology

The efficacy of Fludeoxyglucose F 18 Injection in positron emission tomography cancer imaging was demonstrated in 16 independent studies. These studies prospectively evaluated the use of Fludeoxyglucose F 18 in patients with suspected or known malignancies, including non-small cell lung cancer, colo-rectal, pancreatic, breast, thyroid, melanoma, Hodgkin's and non-Hodgkin's lymphoma, and various types of metastatic cancers to lung, liver, bone, and axillary nodes. All these studies had at least 50 patients and used pathology as a standard of truth. The Fludeoxyglucose F 18 Injection doses in the studies ranged from 200 MBq to 740 MBq with a median and mean dose of 370 MBq.

In the studies, the diagnostic performance of Fludeoxyglucose F 18 Injection varied with the type of cancer, size of cancer, and other clinical conditions. False negative and false positive scans were observed. Negative Fludeoxyglucose F 18 Injection PET scans do not exclude the diagnosis of cancer. Positive Fludeoxyglucose F 18 Injection PET scans cannot replace pathology to establish a diagnosis of cancer. Non-malignant conditions such as fungal infections, inflammatory processes and benign tumors have patterns of increased glucose metabolism that may give rise to false-positive scans. The efficacy of Fludeoxyglucose F 18 Injection PET imaging in cancer screening was not studied.

14.2 Cardiology

The efficacy of Fludeoxyglucose F 18 Injection for cardiac use was demonstrated in ten independent, prospective studies of patients with coronary artery disease and chronic left ventricular systolic dysfunction who were scheduled to undergo coronary revascularization. Before revascularization, patients underwent PET imaging with Fludeoxyglucose F 18 Injection (74 – 370 MBq, 2 – 10 mCi) and perfusion imaging with other diagnostic radiopharmaceuticals. Doses of Fludeoxyglucose F 18 Injection ranged from 74-370 MBq (2-10 mCi). Segmental, left ventricular, wall-motion assessments of asynergic areas made before revascularization were compared in a blinded manner to assessments made after successful revascularization to identify myocardial segments with functional recovery.

Left ventricular myocardial segments were predicted to have reversible loss of systolic function if they showed Fludeoxyglucose F 18 accumulation and reduced perfusion (i.e., flow-metabolism mismatch). Conversely, myocardial segments were predicted to have irreversible loss of systolic function if they showed reductions in both Fludeoxyglucose F 18 accumulation and perfusion (i.e., matched defects).

Findings of flow-metabolism mismatch in a myocardial segment may suggest that successful revascularization will restore myocardial function in that segment. However, false-positive tests occur regularly, and the decision to have a patient undergo revascularization should not be based on PET findings alone. Similarly, findings of a matched defect in a myocardial segment may suggest that myocardial function will not recover in that segment, even if it is successfully revascularized. However, false-negative tests occur regularly, and the decision to recommend against coronary revascularization, or to recommend a cardiac transplant, should not be based on PET findings alone. The reversibility of segmental dysfunction as predicted with Fludeoxyglucose F 18 PET imaging depends on successful coronary revascularization. Therefore, in patients with a low likelihood of successful revascularization, the diagnostic usefulness of PET imaging with Fludeoxyglucose F 18 Injection is more limited.

14.3 Neurology

In a prospective, open label trial, Fludeoxyglucose F 18 Injection was evaluated in 86 patients with epilepsy. Each patient received a dose of Fludeoxyglucose F 18 Injection in the range of 185-370 MBq (5-10 mCi). The mean age was 16.4 years (range: 4 months - 58 years; of these, 42 patients were less than 12 years and 16 patients were less than 2 years old). Patients had a known diagnosis of complex partial epilepsy and were under evaluation for surgical treatment of their seizure disorder. Seizure foci had been previously identified on ictal EEGs and sphenoidal EEGs. Fludeoxyglucose F 18 Injection PET imaging confirmed previous diagnostic findings in 16% (14/87) of the patients; in 34% (30/87) of the patients, Fludeoxyglucose F 18 Injection PET images provided new findings. In 32% (27/87), imaging with Fludeoxyglucose F 18 Injection was inconclusive. The impact of these imaging findings on clinical outcomes is not known.

Several other studies comparing imaging with Fludeoxyglucose F 18 Injection results to subsphenoidal EEG, MRI and/or surgical findings supported the concept that the degree of hypometabolism corresponds to areas of confirmed epileptogenic foci. The safety and effectiveness of Fludeoxyglucose F 18 Injection to distinguish idiopathic epileptogenic foci from tumors or other brain lesions that may cause seizures have not been established.

16 HOW SUPPLIED/STORAGE AND DRUG HANDLING

Fludeoxyglucose F 18 Injection is supplied in a multi-dose, capped glass vial containing between 0.74 – 14.8 GBq/mL (20 - 400 mCi/mL), of no carrier added 2-deoxy-2-[F 18] fluoro-D-glucose, at end of synthesis, in approximately 20 - 22 mL. The contents of each vial are sterile, pyrogen-free and preservative-free.

NDC 13267-234-45

This radiopharmaceutical is licensed by the State of New York, Department Of Health, Bureau of Environmental Radiation Protection, for distribution to persons licensed pursuant to New York's Regulatory Code for Radioactive material specified in Chapter 1-Part 16 of the State Sanitary Code, as appropriate, or under equivalent licenses of an Agreement State or Licensing State.

Store the Fludeoxyglucose F 18 Injection vial upright in a lead shielded container at 25°C (77°F); excursions permitted to 15º to 30°C (59º to 86°F).

Store and dispose of Fludeoxyglucose F 18 Injection in accordance with the regulations and a general license, or its equivalent, of an Agreement State or a Licensing State.

The expiration date and time are provided on the container label. Use Fludeoxyglucose F 18 Injection within 12 hours from the EOS time.

17 PATIENT COUNSELING INFORMATION

Instruct patients in procedures that increase renal clearance of radioactivity. Encourage patients to:

- drink water or other fluids (as tolerated) in the 4 hours before their PET study.
- void as soon as the imaging study is completed and as often as possible thereafter for at least one hour.

Pregnancy: Advise pregnant women of the risk of fetal exposure to radiation with Fludeoxyglucose F 18 Injection [see Use in Specific Populations (8.1)].

Lactation: Advise lactating women that exposure to Fludeoxyglucose F 18 Injection through breast milk can be minimized by pumping and discarding breast milk and avoiding close (breast) contact with the infant for 9 hours after Fludeoxyglucose F 18 Injection [see Use in Specific Populations (8.2)].

Manufactured and Distributed by:
The Feinstein Institute for Medical Research
Northwell Health
Cyclotron/Radiochemistry Facility
350 Community Drive
Manhasset, New York, 11030